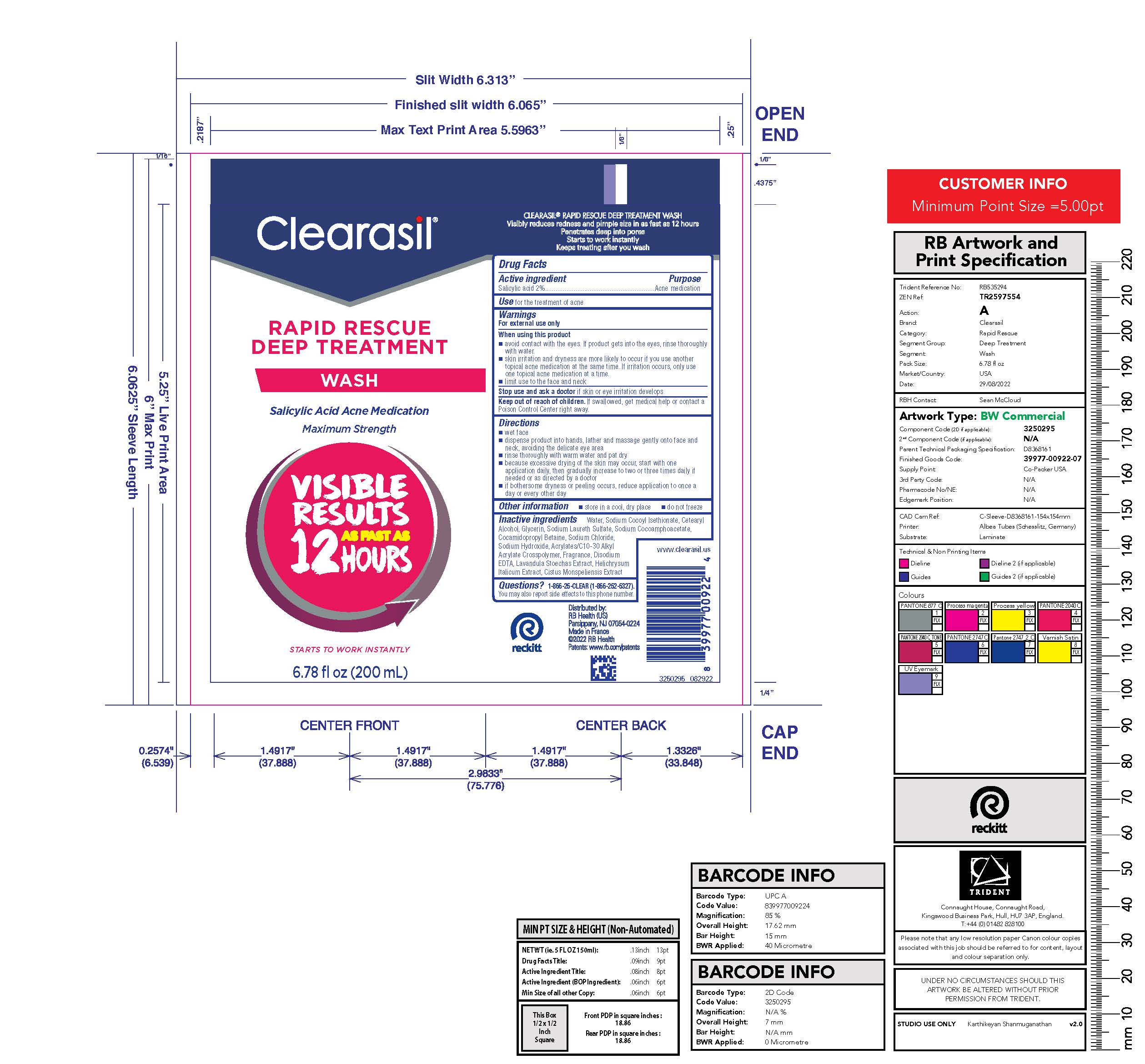 DRUG LABEL: Clearasil Rapid Rescue Deep Treatment Wash
NDC: 63824-432 | Form: LOTION
Manufacturer: RB Health (US) LLC
Category: otc | Type: HUMAN OTC DRUG LABEL
Date: 20241218

ACTIVE INGREDIENTS: SALICYLIC ACID 2 g/100 mL
INACTIVE INGREDIENTS: WATER; SODIUM COCOYL ISETHIONATE; CETOSTEARYL ALCOHOL; GLYCERIN; SODIUM LAURETH-3 SULFATE; SODIUM COCOAMPHOACETATE; COCAMIDOPROPYL BETAINE; SODIUM HYDROXIDE; CARBOMER INTERPOLYMER TYPE A (ALLYL SUCROSE CROSSLINKED); EDETATE DISODIUM ANHYDROUS; HELICHRYSUM ITALICUM FLOWER

Clearasil®Rapid Rescue Deep Treatment Wash

Drug Facts

Active ingredient

Salicylic acid 2%

Purpose

Acne medication

Use

for the treatment of acne

Warnings

For external use only

When using this product

- avoid contact with the eyes. If product gets into the eyes, rinse thoroughly with water.
- skin irritation and dryness is more likely to occur if you use another topical acne medication at the same time. If irritation occurs, only use one topical acne medication at a time.
- limit use to the face and neck

Stop use and ask a doctorif skin or eye irritation develops

Keep out of reach of children.If swallowed, get medical help or contact a Poison Control Center right away.

Directions

- wet face
- dispense product into hands, lather and massage gently onto face and neck, avoiding the delicate eye area
- rinse thoroughly with warm water and pat dry
- because excessive drying of the skin may occur, start with one application daily, then gradually increase to two or three times daily if needed or as directed by a doctor
- if bothersome dryness or peeling occurs, reduce application to once a day or every other day

Other information

- store in a cool, dry place
- do not freeze

Inactive ingredients

Water, Sodium Cocoyl Isethionate, Cetearyl Alcohol, Glycerin, Sodium Laureth Sulfate, Sodium Cocoamphoacetate, Cocamidopropyl Betaine, Sodium Hydroxide, Acrylates/C10-30 Alkyl Acrylate Crosspolymer, Fragrance, Disodium EDTA, Lavendula Stoechas Extract, Helichrysum Italicum Extract, Cistus Monspeliensis Extract

Questions?

1-866-25-CLEAR (1-866-252-5327).You may also report side effects to this phone number.

Distributed By:
RB Health (US),
Parsippany, NJ 07054-0224
Made in France

PRINCIPAL DISPLAY PANEL - 200 mL Tube Label

Clearasil®

RAPID RESCUE
DEEP TREATMENT

WASH

Salicylic Acid Acne Medication

Maximum Strength

VISIBLE
RESULTS
AS FAST AS
12 HOURS

STARTS TO WORK INSTANTLY

6.78 fl oz (200 mL)